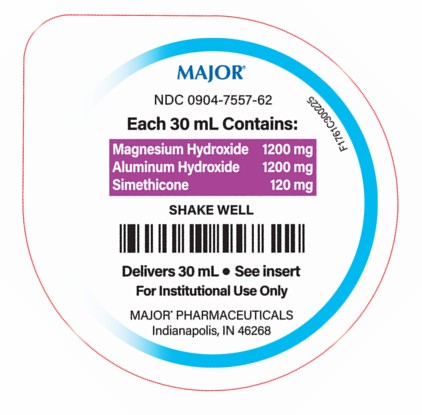 DRUG LABEL: Aluminum Hydroxide, Magnesium Hydroxide, and Simethicone
NDC: 0904-7557 | Form: SUSPENSION
Manufacturer: Major Pharmaceuticals
Category: otc | Type: HUMAN OTC DRUG LABEL
Date: 20250707

ACTIVE INGREDIENTS: ALUMINUM HYDROXIDE 1200 mg/30 mL; MAGNESIUM HYDROXIDE 1200 mg/30 mL; DIMETHICONE 120 mg/30 mL
INACTIVE INGREDIENTS: BUTYLPARABEN; PROPYLPARABEN; PROPYLENE GLYCOL; SORBITOL; SACCHARIN SODIUM; PEPPERMINT OIL; WATER; HYDROXYPROPYL METHYLCELLULOSE

Aluminum Hydroxide, Magnesium Hydroxide, and Simethicone Suspension

Drug Facts

Active ingredients Purpose
(in each 5 mL = 1 teaspoonful)

Aluminum hydroxide (equiv. to dried gel, USP) 200 mg .......................... Antacid
Magnesium hydroxide 200 mg .............................................................. Antacid
Simethicone 20 mg ............................................................................... Antigas

INDICATIONS AND USAGE

Uses for the relief of:

- acid indigestion
- heartburn
- sour stomach
- upset stomach due to these symptoms
- pressure and bloating commonly referred to as gas

Warnings

Do not take more than 16 teaspoonfuls in a 24-hour period or use the maximum dosage for more than 2 weeks except under the advice and supervision of a physician.

Ask a doctor before use if you have

- kidney disease
- a magnesium-restricted diet

Ask a doctor or pharmacist before use if you are presently taking a prescription drug. Antacids may interact with certain prescription drugs.

Stop use and ask a doctor if symptoms last more than 2 weeks.

Keep out of reach of children.

Directions

- shake well before using
- do not take more than 16 teaspoonfuls in 24 hours or use the maximum dosage for more than 2 weeks

adults and children 12 years and older | take 2 to 4 teaspoonfuls four times a day or as directed by a physician
children under 12 years | consult a physician

Other information

- each 5 mL contains: magnesium 83 mg, sodium 1.34 mg
- store at controlled room temperature 20° - 25°C (68° - 77°F) {See USP Controlled Room Temperature].
- protect from freezing
- White colored, peppermint flavored liquid supplied in the following oral dosage form:

NDC 0904-7557-62: 30 mL unit dose cup, in a tray of ten cups.

INACTIVE INGREDIENT

Inactive ingredients butylparaben, hydroxypropyl methylcellulose, flavoring, propylene glycol, propylparaben, purified water, saccharin sodium, and sorbitol solution.

R02/25

Distributed by:
MAJOR® PHARMACEUTICALS
Indianapolis, IN 46268

PRINCIPAL DISPLAY PANEL - 30 mL Unit-Dose Cup Lidding Label

MAJOR®
NDC 0904-7557-62

Each 30 mL Contains:

Magnesium Hydroxide 1200 mg
Aluminum Hydroxide 1200 mg
Simethicone 120 mg

SHAKE WELL

Delivers 30 mL • See insert

For Institutional Use Only

MAJOR® PHARMACEUTICALS
Indianapolis, IN 46268